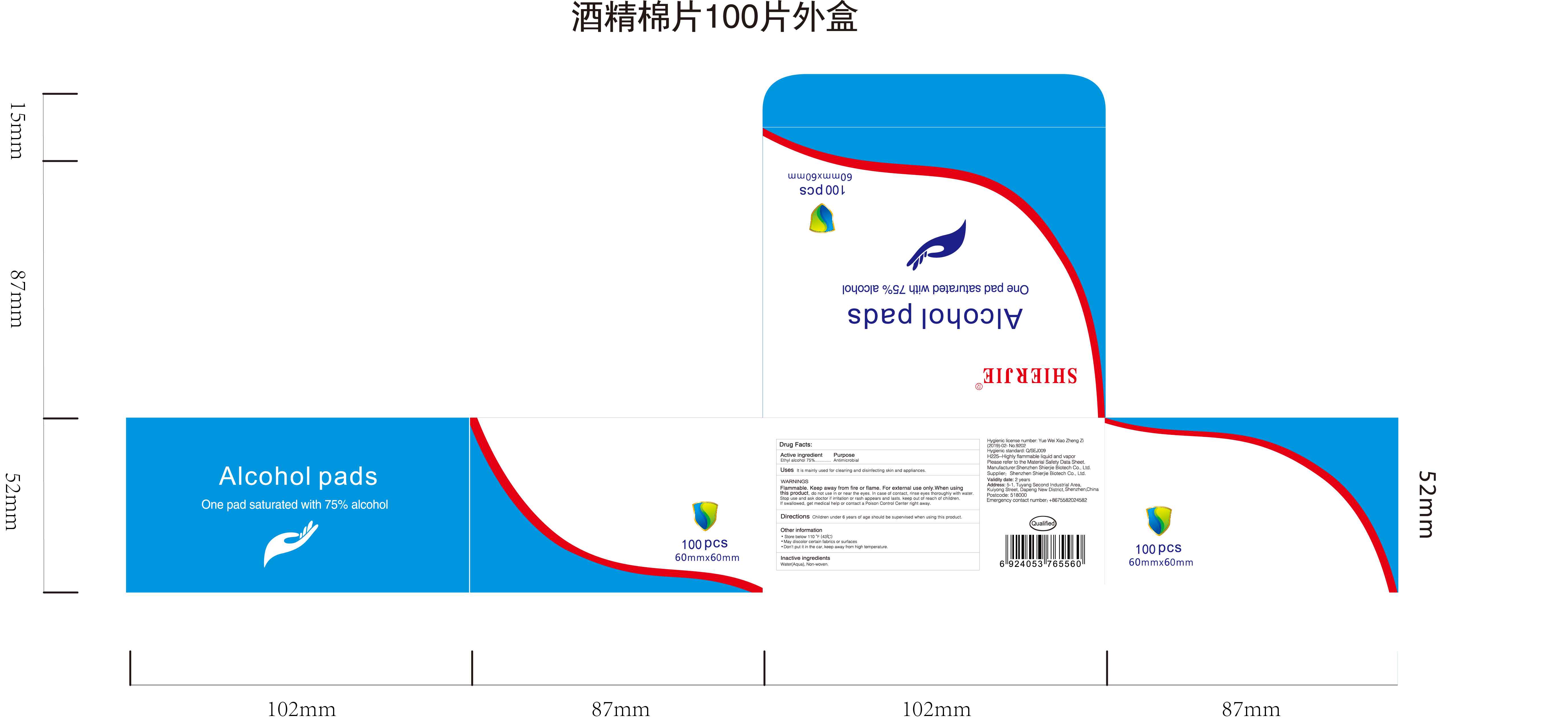 DRUG LABEL: SHIERJIE 75% Alcohol Pads
NDC: 43116-016 | Form: CLOTH
Manufacturer: Shenzhen Shierjie Biological Engineering Co., LTD
Category: otc | Type: HUMAN OTC DRUG LABEL
Date: 20201122

ACTIVE INGREDIENTS: ALCOHOL 75 mL/100 1
INACTIVE INGREDIENTS: WATER

43116-016
SHIERJIE 75% Alcohol Pads

Active Ingredient

Ethyl Alcohol 75%

Purpose

Antimicrobial

Uses

It is mainly used for cleaning and disinfecting skin and appliances

Warnings

Flammable. Keep away from fire or flame, For external use only.When using this product,do not use in or near the eyes.In case of contact,rinse eyes thoroughly with water.Stop use and ask doctor if irritation or rash appears and lasts,Keep out of reach for children if swallowed,get medical help of contact a Poison Control Center right away.

Directions

Children under 6 years of age should be supervised when using this product

Other information

Store below 110°(43°C)

May discolor certain fabrics or surfaces

Inactive ingredients

Water(Aqua),Non-woven